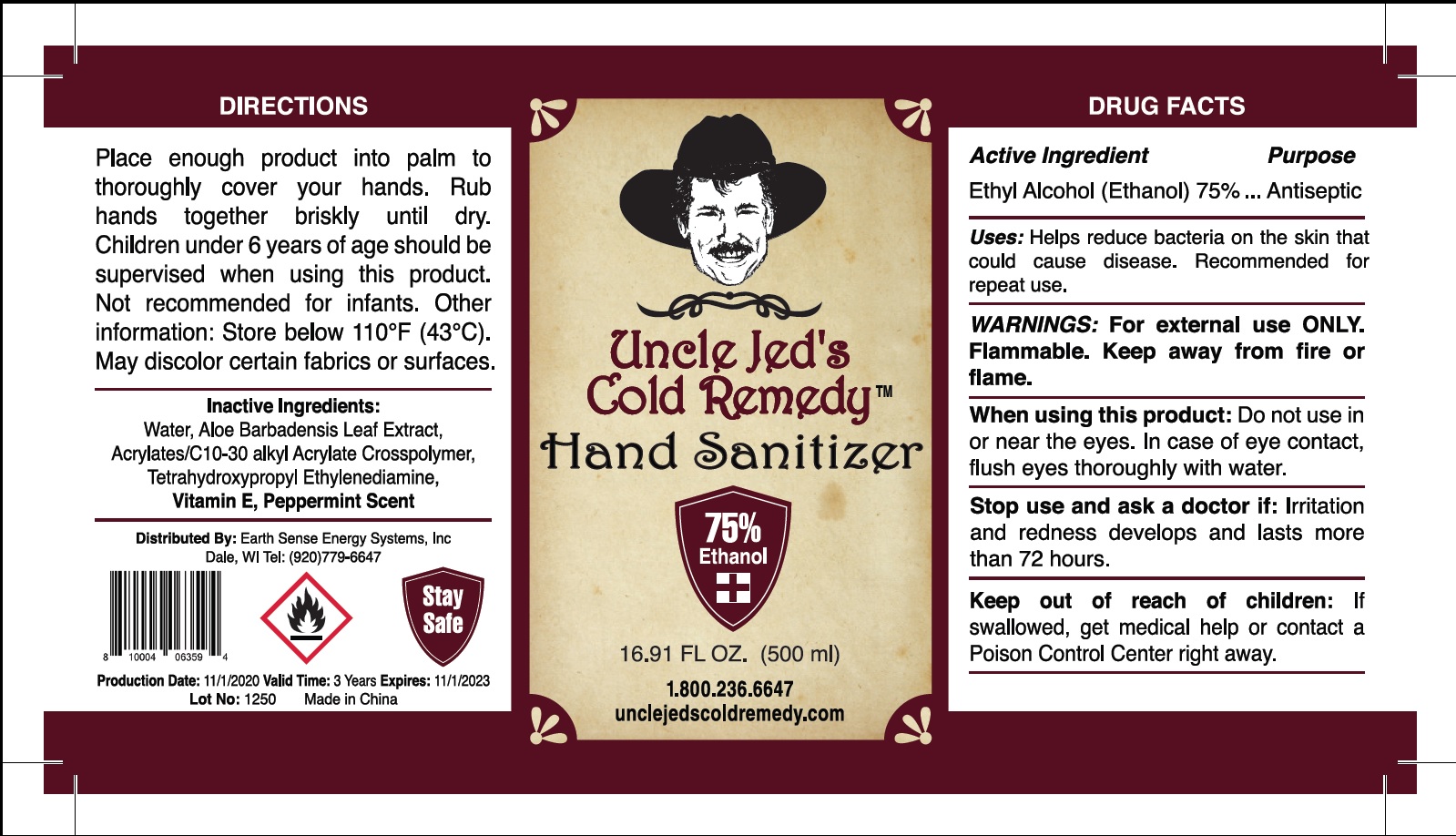 DRUG LABEL: Uncle Jeds Cold Remedy Hand Sanitizer
NDC: 81172-000 | Form: GEL
Manufacturer: EARTH SENSE ENERGY SYSTEMS, INC
Category: otc | Type: HUMAN OTC DRUG LABEL
Date: 20201127

ACTIVE INGREDIENTS: ALCOHOL 0.75 mL/1 mL
INACTIVE INGREDIENTS: WATER; ALOE VERA LEAF; CARBOMER INTERPOLYMER TYPE A (ALLYL SUCROSE CROSSLINKED); EDETOL; .ALPHA.-TOCOPHEROL

Uncle Jeds Cold Remedy Hand Sanitizer

Active Ingredient

Ethyl Alcohol (Ethanol) 75%

Purpose

Antiseptic

Uses:

Helps reduce bacteria on the skin that could cause disease. Recommended for repeat use.

WARNINGS:

For external use ONLY. Flammable. Keep away from fire or flame.

When using this product:

Do not use in or near the eyes. In case of eye contact, flush eyes thoroughly with water.

Stop use and ask a doctor if:

Irritation and redness develops and lasts more than 72 hours.

Keep out of reach of children:

If swallowed, get medical help or contact a Poison Control Center right away.

DIRECTIONS

Place enough product into palm to thoroughly cover your hands. Rub hands together briskly until dry. Children under 6 years of age should be
supervised when using this product. Not recommended for infants. Other information: Store below 110°F (43°C). May discolor certain fabrics or
surfaces.

Inactive Ingredients:

Water, Aloe Barbadensis Leaf Extract, Acrylates/C10-30 alkyl Acrylate Crosspolymer, Tetrahydroxypropyl Ethylenediamine, Vitamin E, Peppermint Scent.